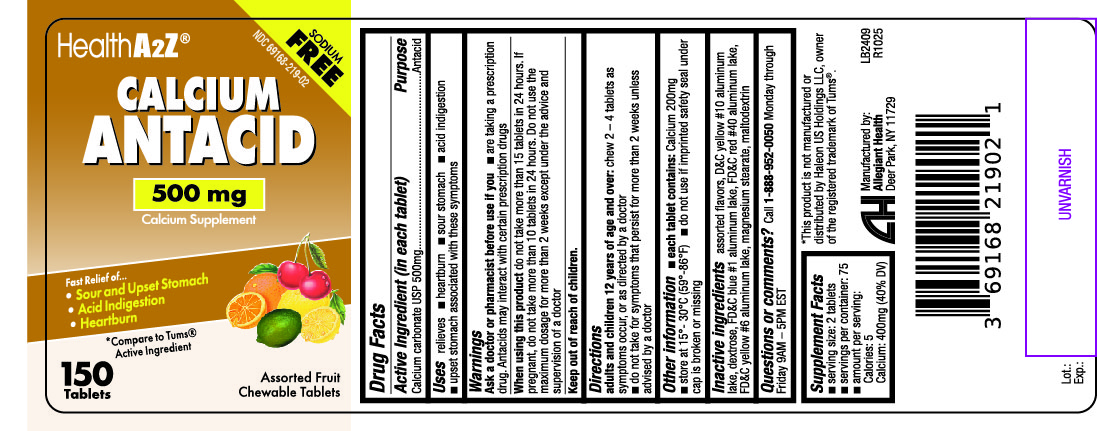 DRUG LABEL: Calcium Antacid
NDC: 69168-219 | Form: TABLET, CHEWABLE
Manufacturer: Allegiant Health
Category: otc | Type: HUMAN OTC DRUG LABEL
Date: 20171108

ACTIVE INGREDIENTS: CALCIUM CARBONATE 500 mg/1 1
INACTIVE INGREDIENTS: FD&C BLUE NO. 1; DEXTROSE; MAGNESIUM STEARATE; MALTODEXTRIN; FD&C RED NO. 40; FD&C YELLOW NO. 6; D&C YELLOW NO. 10

Drug Facts

Active ingredient (in each tablet)

Calcium Carbonate 500 mg

Purpose

Antacid

Uses

relieves

- heartburn
- sour stomach
- acid indigestion
- upset stomach associated with these symptoms

Warnings

Ask a doctor or pharmacist before use if you

- have kidney disease
- are taking a prescription drug. Antacids may interact with certain prescription drugs

When using this product

- do not take more than 15 tablets in 24 hours
- if pregnant, do not take more than 10 tablets in 24 hours
- do not use the maximum dosage for more than 2 weeks except under the advice and supervision of a doctor

Directions

- adults and children 12 years of age and over: chew 2 – 4 tablets as symptoms occur, or as directed by a doctor
- do not take for symptoms that persist for more than 2 weeks unless advised by a doctor

Other information

- each tablet contains: calcium 200mg
- store at 15º-30ºC (59º-86ºF)
- do not use if imprinted safety seal under cap is broken or missing

Inactive ingredients

assorted flavors, D&C yellow #10 aluminum lake, dextrose, FD&C blue #1 aluminum lake, FD&C red #40 aluminum lake, FD&C yellow #6 aluminum lake, magnesium stearate, maltodextrin

Package/Label Principal Display Panel

Calcium Antacid 500mg
SODIUM FREE

Health A2Z®

CALCIUM ANTACID
500 mg
Calcium Supplement

Fast Relief of...

- Sour & Upset Stomach
- Acid Indigestion
- Heartburn

*Compare to Tums® Active Ingredient

Assorted Fruit

Chewable Tablets